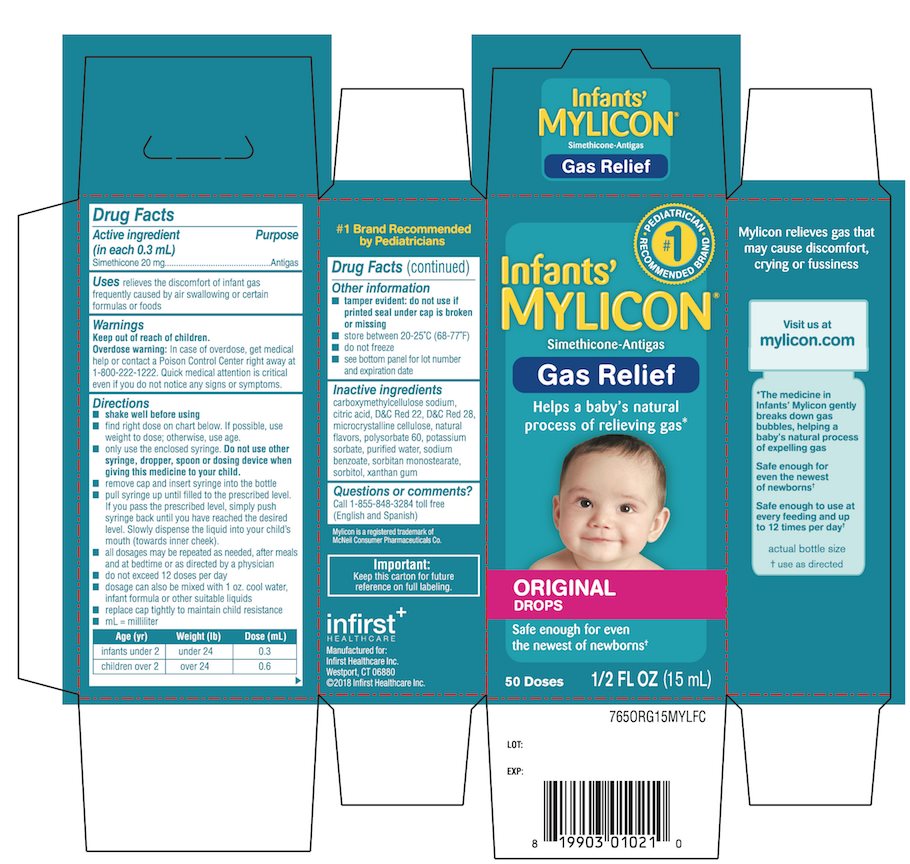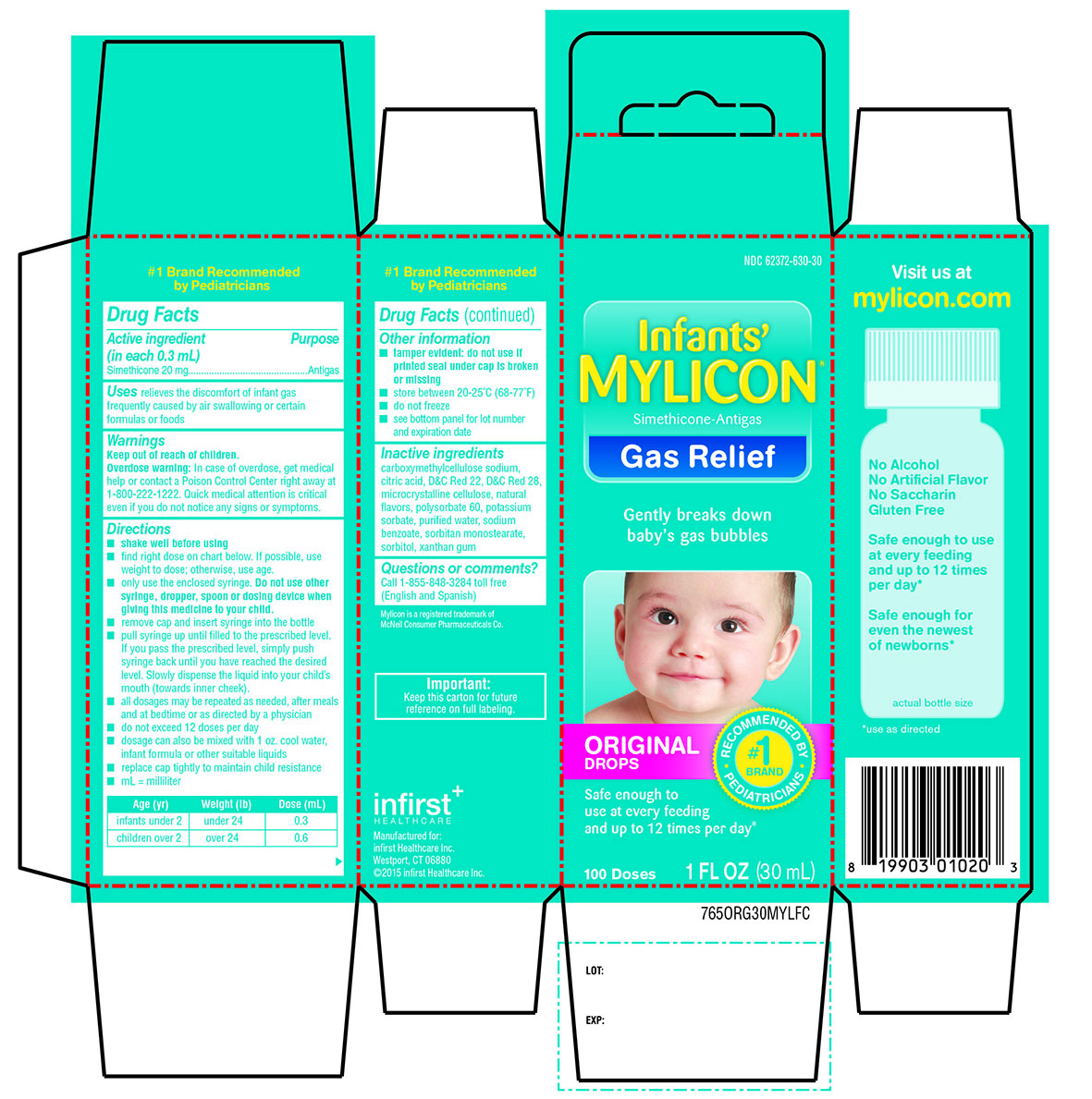 DRUG LABEL: Mylicon Infants Gas Relief Original
NDC: 62372-630 | Form: EMULSION
Manufacturer: Infirst Healthcare
Category: otc | Type: HUMAN OTC DRUG LABEL
Date: 20240101

ACTIVE INGREDIENTS: DIMETHICONE 20 mg/0.3 mL
INACTIVE INGREDIENTS: CARBOXYMETHYLCELLULOSE SODIUM, UNSPECIFIED FORM; ANHYDROUS CITRIC ACID; D&C RED NO. 22; D&C RED NO. 28; MICROCRYSTALLINE CELLULOSE; POLYSORBATE 60; POTASSIUM SORBATE; WATER; SODIUM BENZOATE; SORBITAN MONOSTEARATE; SORBITOL; XANTHAN GUM

Infant’s Mylicon Gas Relief Original

Active ingredient (in each 0.3 mL)

Simethicone 20 mg

Purpose

Antigas

Uses

relieves the discomfort of infant gas frequently caused by air swallowing or certain formulas or foods

Warnings

Keep out of reach of children.

Overdose warning: In case of overdose get medical help or contact a Poison Control Center right away at 1-800-222-1222. Quick medical attention is critical even if you do not notice any signs or symptoms.

Directions

- shake well before using
- find right dose on chart below. If possible, use weight to dose; otherwise, use age.
- only use the enclosed syringe. Do not use other syringe, dropper, spoon or dosing device when giving this medicine to your child.
- remove cap and insert syringe into the bottle
- pull syringe up until filled to the prescribed level. If you pass the prescribed level, simply push syringe back until you have reached the desired level. Slowly dispense the liquid into your child’s mouth (toward inner cheek).
- all dosages may be repeated as needed, after meals and at bedtime or as directed by a physician.
- do not exceed 12 doses per day.
- dosage can also be mixed with 1 oz. cool water, infant formula or other suitable liquids
- replace cap tightly to maintain child resistance
- mL = milliliter

Age (yr) | Weight (lb) | Dose (mL)
infants under 2 | under 24 | 0.3
children over 2 | over 24 | 0.6

Other information

- tamper evident: do not use if printed seal under cap is broken or missing
- store between 20-25°C (68-77°F)
- do not freeze
- see bottom panel for lot number and expiration date

Inactive ingredients

carboxymethylcellulose sodium, citric acid, D&C Red 22, D&C Red 28, microcrystalline cellulose, natural flavors, polysorbate 60, potassium sorbate, purified water, sodium benzoate, sorbitan monostearate, sorbitol, xanthan gum

Questions or comments?

Call 1-855-848-3284 toll free (English and Spanish)

Principal Display Panel

Infants' Mylicon®

Simethicone-Antigas

Gas Relief

Gently breaks down baby’s gas bubbles

Original Drops

Non-staining

Safe enough to use at every feeding and up to 12 times per day*

#1 Brand

Recommended by Pediatricians

1 Fl. OZ (30ml)

100 Doses

Visit us at mylicon.com

No Alcohol

No Artificial Flavors

No Saccharin

Gluten Free

Safe enough to use at every feeding and up to 12 times per day*

Safe enough for even the newest of newborns*

*use as directed

Mylicon is a registered trademark of McNeil Consumer Pharmaceuticals Co.

Important: Keep this carton for future reference on full labeling

Manufactured for

infirst Healthcare Inc.

Westport, CT 06880

©2015 infirst Healthcare Inc.

Package Label for 30 mL

Package Label for 15 mL